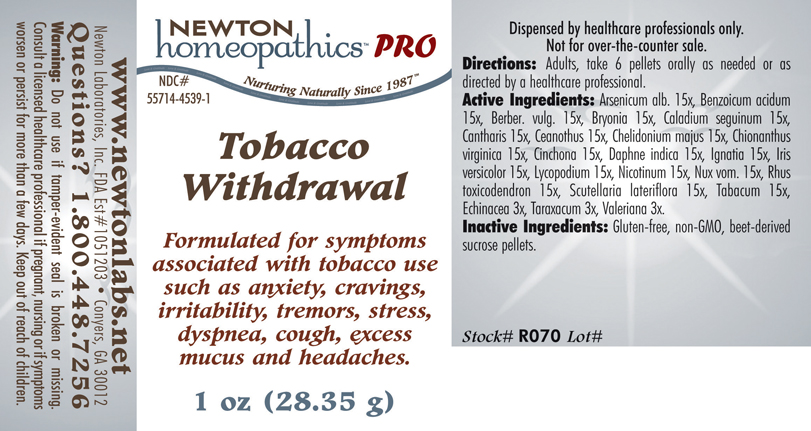 DRUG LABEL: Tobacco Withdrawal 
NDC: 55714-4539 | Form: PELLET
Manufacturer: Newton Laboratories, Inc.
Category: homeopathic | Type: HUMAN PRESCRIPTION DRUG LABEL
Date: 20110601

ACTIVE INGREDIENTS: Arsenic Trioxide 15 [hp_X]/1 g; Benzoic Acid 15 [hp_X]/1 g; Berberis Vulgaris Root Bark 15 [hp_X]/1 g; Bryonia Alba Root 15 [hp_X]/1 g; Dieffenbachia Seguine 15 [hp_X]/1 g; Lytta Vesicatoria 15 [hp_X]/1 g; Ceanothus Americanus Leaf 15 [hp_X]/1 g; Chelidonium Majus 15 [hp_X]/1 g; Chionanthus Virginicus Bark 15 [hp_X]/1 g; Cinchona Officinalis Bark 15 [hp_X]/1 g; Daphne Odora Bark 15 [hp_X]/1 g; Strychnos Ignatii Seed 15 [hp_X]/1 g; Iris Versicolor Root 15 [hp_X]/1 g; Lycopodium Clavatum Spore 15 [hp_X]/1 g; Nicotine 15 [hp_X]/1 g; Strychnos Nux-vomica Seed 15 [hp_X]/1 g; Toxicodendron Pubescens Leaf 15 [hp_X]/1 g; Scutellaria Lateriflora 15 [hp_X]/1 g; Tobacco Leaf 15 [hp_X]/1 g; Echinacea, Unspecified 3 [hp_X]/1 g; Taraxacum Officinale 3 [hp_X]/1 g; Valerian 3 [hp_X]/1 g
INACTIVE INGREDIENTS: Sucrose

Tobacco Withdrawal

INDICATIONS & USAGE SECTION

Tobacco Withdrawal Formulated for symptoms associated with tobacco use such as anxiety, cravings, irritability, tremors, stress, dyspnea, cough, excess mucus and headaches.

DOSAGE & ADMINISTRATION SECTION

Directions: Adults, take 6 pellets orally as needed or as directed by a healthcare professional.

ACTIVE INGREDIENT SECTION

Arsenicum alb. 15x, Benzoicum acidum 15x, Berber. vulg. 15x, Bryonia 15x, Caladium seguinum 15x, Cantharis 15x, Ceanothus 15x, Chelidonium majus 15x, Chionanthus virginica 15x, Cinchona 15x, Daphne indica 15x, Ignatia 15x, Iris versicolor 15x, Lycopodium 15x, Nicotinum 15x, Nux vom. 15x, Rhus toxicodendron 15x, Scutellaria lateriflora 15x, Tabacum 15x, Echinacea 3x, Taraxacum 3x, Valeriana 3x.

PURPOSE SECTION

Formulated for symptoms associated with tobacco use such as anxiety, cravings, irritability, tremors, stress, dyspnea, cough, excess mucus and headaches.

INACTIVE INGREDIENT SECTION

Inactive Ingredients: Gluten-free, non-GMO, beet-derived sucrose pellets.

QUESTIONS? SECTION

www.newtonlabs.net Newton Laboratories, Inc. FDA Est # 1051203 - Conyers, GA 30012
Questions? 1.800.448.7256

WARNINGS SECTION

Warning: Do not use if tamper - evident seal is broken or missing. Consult a licensed healthcare professional if pregnant, nursing or if symptoms worsen or persist for more than a few days. Keep out of reach of children.

PREGNANCY OR BREAST FEEDING SECTION

Consult a licensed healthcare professional if pregnant, nursing or if symptoms worsen or persist for more than a few days

KEEP OUT OF REACH OF CHILDREN SECTION

Keep out of reach of children.